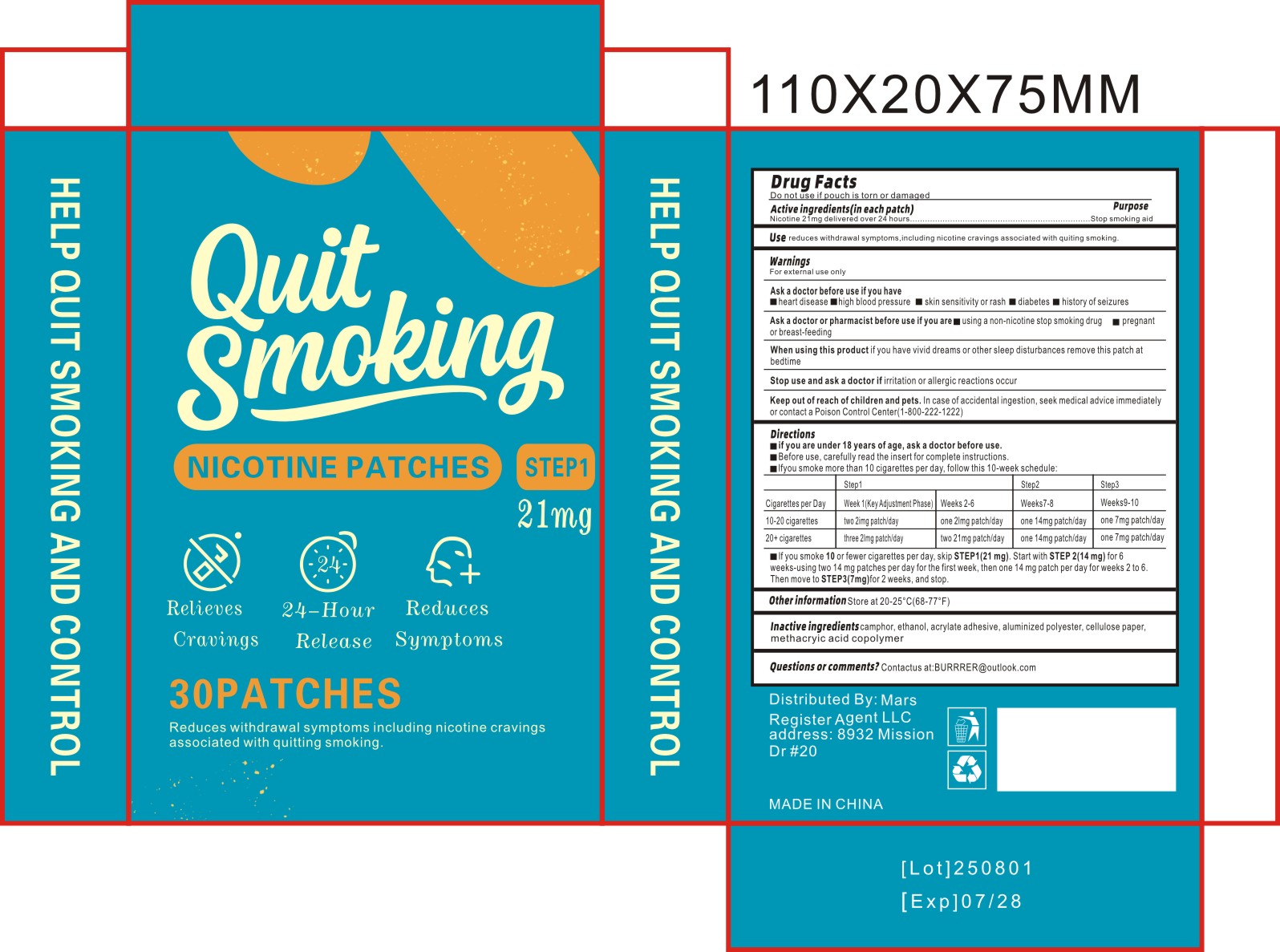 DRUG LABEL: Nicotine Patches
NDC: 85795-002 | Form: PATCH
Manufacturer: Shenzhen TeLaFaErJiaLuo Technology Co., Ltd.
Category: otc | Type: HUMAN OTC DRUG LABEL
Date: 20250717

ACTIVE INGREDIENTS: NICOTINE 21 mg/100 1
INACTIVE INGREDIENTS: ACRYLIC ACID; CAMPHOR, (-)-; ALUMINUM POWDER; METHACRYLIC ACID; ALCOHOL; POWDERED CELLULOSE

85795-002

Active Ingredient

Nicotine 21mg

Purpose

Stop smoking aid

Use

reduces withdrawal symptoms, including nicotine cravings associated with quitting smoking.

Warnings

For external use only

Do not use

heart disease , high blood pressure , skin sensitivity or rash , diabetes , history of seizures

When Using

if you have vivid dreams or other sleep disturbances remove this patch at bedtime

Stop Use

if irritation or allergic reactions occur

Ask Doctor

using a non-nicotine stop smoking drug , pregnant or breast-feeding

Keep Out Of Reach Of Children

In case of accidental ingestion,seek medical advice immediatelyor contact aPoison Control Center(1-800-222-1222)

Directions

if you are under 18 years of age,ask a doctor before use.
Before use,carefully read the insert for complete instructions.
Ifyou smoke more than 10 cigarettes per day,follow this 10-week schedule:
lf you smoke 10 or fewer cigarettes per day,skip STEP1(21 mg).Start with STEP 2(14 mg)for 6
weeks-using two 14 mg patches per day for the first week,then one 14 mg patch per day for weeks 2 to 6.Then move to STEP3(7mg)for 2 weeks,and stop.

Other information

Store at 20-25°℃(68-77°F)

Inactive ingredients

camphor , ethanol , acrylate adhesive , aluminized polyester , cellulose paper , methacryic acid copolymer

Questions

Contactus at:BURRRER@outlook.com